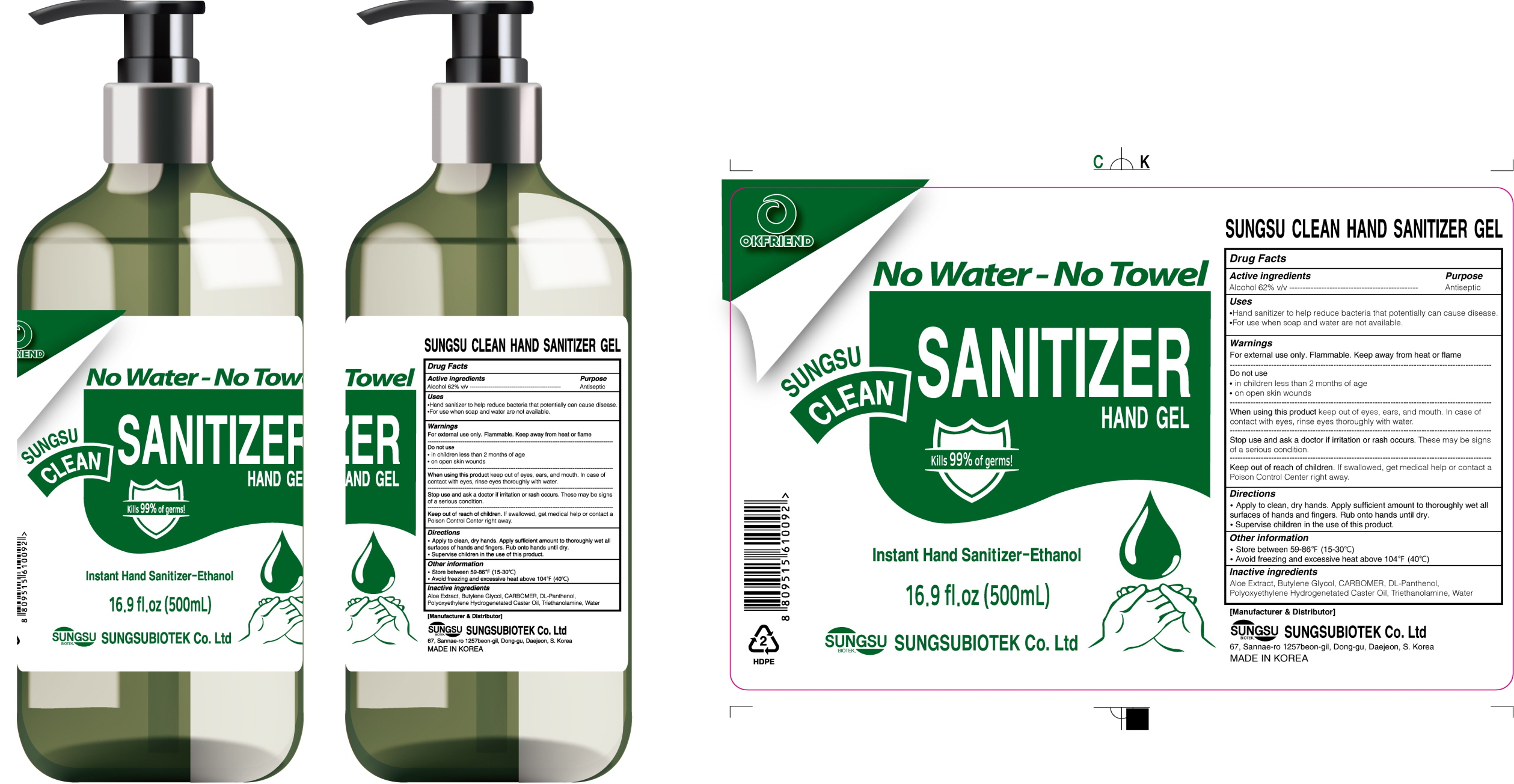 DRUG LABEL: SUNGSU Clean Hand Sanitizer
NDC: 80454-030 | Form: GEL
Manufacturer: SUNGSUBIOTEK CO. LTD.
Category: otc | Type: HUMAN OTC DRUG LABEL
Date: 20200911

ACTIVE INGREDIENTS: Alcohol 310 mL/500 mL
INACTIVE INGREDIENTS: ALOE; Butylene Glycol; CARBOMER HOMOPOLYMER, UNSPECIFIED TYPE; PANTHENOL; TROLAMINE; Water

ACTIVE INGREDIENT

Alcohol 62% v/v

INACTIVE INGREDIENTS

Aloe Extract, Butylene Glycol, CARBOMER, DL-Panthenol, Polyoxyethylene Hydrogenetated Caster Oil, Triethanolamine, Water

PURPOSE

Antiseptic

WARNINGS

For external use only. Flammable. Keep away from heat or flame
--------------------------------------------------------------------------------------------------------
Do not use
• in children less than 2 months of age
• on open skin wounds
--------------------------------------------------------------------------------------------------------
When using this product keep out of eyes, ears, and mouth. In case of contact with eyes, rinse eyes thoroughly with water.
--------------------------------------------------------------------------------------------------------
Stop use and ask a doctor if irritation or rash occurs. These may be signs of a serious condition.

Keep out of reach of children. If swallowed, get medical help or contact a Poison Control Center right away.

Uses

• Hand sanitizer to help reduce bacteria that potentially can cause disease.
• For use when soap and water are not available.

Directions

• Apply to clean, dry hands. Apply sufficient amount to thoroughly wet all surfaces of hands and fingers. Rub onto hands until dry.
• Supervise children in the use of this product.

Other information

• Store between 59-86℉ (15-30℃)
• Avoid freezing and excessive heat above 104℉ (40℃)